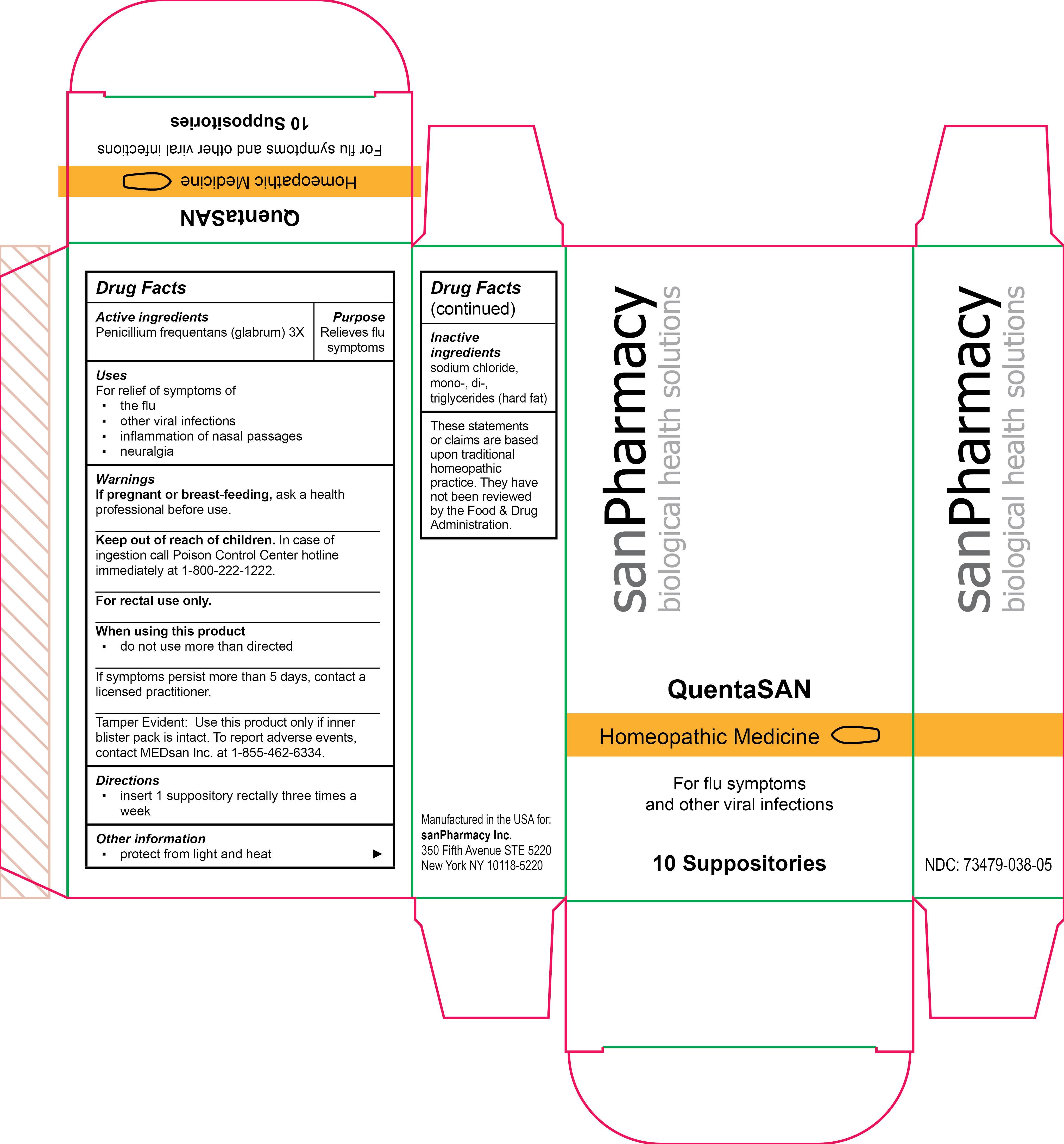 DRUG LABEL: QuentaSAN
NDC: 73479-038 | Form: SUPPOSITORY
Manufacturer: sanPharmacy Inc.
Category: homeopathic | Type: HUMAN OTC DRUG LABEL
Date: 20231220

ACTIVE INGREDIENTS: PENICILLIUM GLABRUM 3 [hp_X]/1 1
INACTIVE INGREDIENTS: FAT, HARD; WATER; SODIUM CHLORIDE

QuentaSAN Suppositories

Indications

For flu symptoms and other viral infections

PURPOSE

Relieves flu symptoms

Ingredients

Penicillium frequentans (glabrum) 3X

INACTIVE INGREDIENT

sodium chloride, mono-, di-, triglycerides (hard fat)

Dosage

insert 1 suppository rectally three times a week

Warning

If pregnant or breast-feeding, ask a health professional before use.
______________________________
Keep out of reach of children. In case of ingestion call Poison Control Center hotline immediately at 1-800-222-1222.
______________________________
For rectal use only.
______________________________
When using this product
▪ do not use more than directed
______________________________
If symptoms persist more than 5 days, contact a licensed practitioner.
______________________________
Tamper Evident: Use this product only if inner blister pack is intact. To report adverse events, contact MEDsan Inc. at 1-855-462-6334.

Keep out of reach of children. In case of ingestion call Poison Control Center hotline immediately at 1-800-222-1222.

Tamper Evident

Tamper Evident: Use this product only if inner blister pack is intact. To report adverse events, contact MEDsan Inc. at 1-855-462-6334.

Manufactured in the USA for:
sanPharmacy Inc.
350 Fifth Avenue STE 5220
New York NY 10118-5220

RECENT MAJOR CHANGES

Indications and Usage

Dosage and Administration

Warnings and Precautions

STORAGE AND HANDLING

▪protect from light and heat

Liability Statement

These statements or claims are based upon traditional homeopathic practice. They have not been reviewed by the Food & Drug Administration.

PRINCIPAL DISPLAY PANEL

QuentaSAN

Homeopathic Medicine

For flu symptoms and other viral infections

10 Suppositories

sanPharmacy
biological health solutions